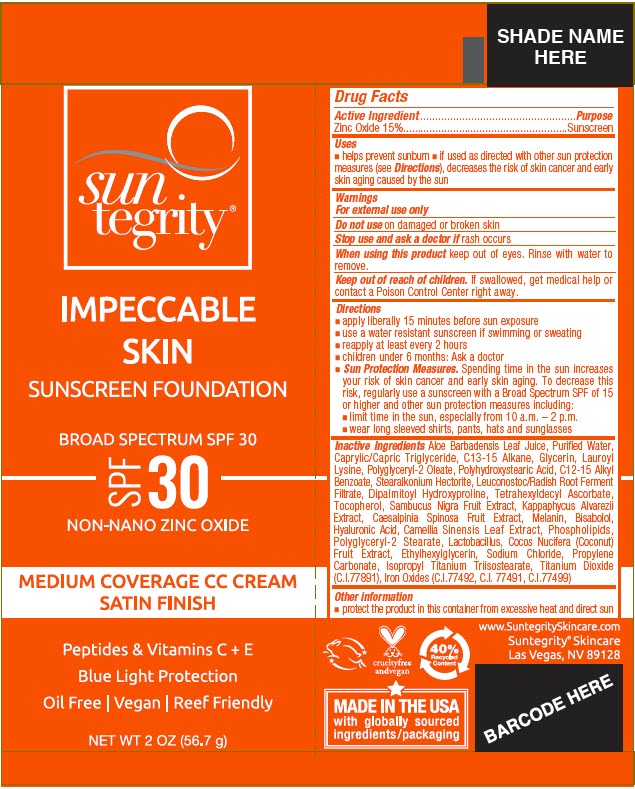 DRUG LABEL: IMPECCABLE SKIN - IVORY
NDC: 69949-151 | Form: CREAM
Manufacturer: Synchronicity Spa, Inc. DBA Suntegrity
Category: otc | Type: HUMAN OTC DRUG LABEL
Date: 20241121

ACTIVE INGREDIENTS: ZINC OXIDE 150 mg/1 g
INACTIVE INGREDIENTS: ALOE VERA LEAF; WATER; MEDIUM-CHAIN TRIGLYCERIDES; C13-15 ALKANE; GLYCERIN; LAUROYL LYSINE; POLYGLYCERYL-2 OLEATE; POLYHYDROXYSTEARIC ACID STEARATE; ALKYL (C12-15) BENZOATE; STEARALKONIUM HECTORITE; LEUCONOSTOC/RADISH ROOT FERMENT FILTRATE; DIPALMITOYL HYDROXYPROLINE; TETRAHEXYLDECYL ASCORBATE; TOCOPHEROL; EUROPEAN ELDERBERRY; KAPPAPHYCUS ALVAREZII; TARA SPINOSA FRUIT POD; MELANIN SYNTHETIC (TYROSINE, PEROXIDE); .ALPHA.-BISABOLOL, (+/-)-; HYALURONIC ACID; GREEN TEA LEAF; OMEGA-3 FATTY ACIDS; POLYGLYCERYL-2 STEARATE; BIFIDOBACTERIUM ANIMALIS LACTIS; COCONUT; ETHYLHEXYLGLYCERIN; SODIUM CHLORIDE; PROPYLENE CARBONATE; ISOPROPYL TITANIUM TRIISOSTEARATE; TITANIUM DIOXIDE; FERROSOFERRIC OXIDE; FERRIC OXIDE RED; FERRIC OXIDE YELLOW

IMPECCABLE SKIN

Drug Facts

Active Ingredient

Zinc Oxide 15%

Purpose

Sunscreen

Uses

- helps prevent sunburn
- if used as directed with other sun protection measures (see Directions), decreases the risk of skin cancer and early skin aging caused by the sun

Warnings

For external use only

Do not use on damaged or broken skin

Stop use and ask a doctor if rash occurs

When using this product keep out of eyes. Rinse with water to remove.

Keep out of reach of children. If swallowed, get medical help or contact a Poison Control Center right away.

Directions

- apply liberally 15 minutes before sun exposure
- use a water resistant sunscreen if swimming or sweating
- reapply at least every 2 hours
- children under 6 months: Ask a doctor
- Sun Protection Measures. Spending time in the sun increases your risk of skin cancer and early skin aging. To decrease this risk, regularly use a sunscreen with a Broad Spectrum SPF of 15 or higher and other sun protection measures including:
  - limit time in the sun, especially from 10 a.m. – 2 p.m.
  - wear long sleeved shirts, pants, hats and sunglasses

Inactive Ingredients

Aloe Barbadensis Leaf Juice, Purified Water, Caprylic/Capric Triglyceride, C13-15 Alkane, Glycerin, Lauroyl Lysine, Polyglyceryl-2 Oleate, Polyhydroxystearic Acid, C12-15 Alkyl Benzoate, Stearalkonium Hectorite, Leuconostoc/Radish Root Ferment Filtrate, Dipalmitoyl Hydroxyproline, Tetrahexyldecyl Ascorbate, Tocopherol, Sambucus Nigra Fruit Extract, Kappaphycus Alvarezii Extract, Caesalpinia Spinosa Fruit Extract, Melanin, Bisabolol, Hyaluronic Acid, Camellia Sinensis Leaf Extract, Phospholipids, Polyglyceryl-2 Stearate, Lactobacillus, Cocos Nucifera (Coconut) Fruit Extract, Ethylhexylglycerin, Sodium Chloride, Propylene Carbonate, Isopropyl Titanium Triisostearate, Titanium Dioxide (C.I.77891), Iron Oxides (C.I.77492, C.I. 77491, C.I.77499)

Other information

- protect the product in this container from excessive heat and direct sun

PRINCIPAL DISPLAY PANEL - 56.7 g Tube Label - Ivory

sun
tegrity®

IMPECCABLE
SKIN
SUNSCREEN FOUNDATION

BROAD SPECTRUM SPF 30

SPF
30

NON-NANO ZINC OXIDE

MEDIUM COVERAGE CC CREAM
SATIN FINISH

Peptides & Vitamins C + E
Blue Light Protection
Oil Free | Vegan | Reef Friendly

NET WT 2 OZ (56.7 g)

PRINCIPAL DISPLAY PANEL - 56.7 g Tube Label - Buff

sun
tegrity®

IMPECCABLE
SKIN
SUNSCREEN FOUNDATION

BROAD SPECTRUM SPF 30

SPF
30

NON-NANO ZINC OXIDE

MEDIUM COVERAGE CC CREAM
SATIN FINISH

Peptides & Vitamins C + E
Blue Light Protection
Oil Free | Vegan | Reef Friendly

NET WT 2 OZ (56.7 g)

PRINCIPAL DISPLAY PANEL - 56.7 g Tube Label - Sand

sun
tegrity®

IMPECCABLE
SKIN
SUNSCREEN FOUNDATION

BROAD SPECTRUM SPF 30

SPF
30

NON-NANO ZINC OXIDE

MEDIUM COVERAGE CC CREAM
SATIN FINISH

Peptides & Vitamins C + E
Blue Light Protection
Oil Free | Vegan | Reef Friendly

NET WT 2 OZ (56.7 g)

PRINCIPAL DISPLAY PANEL - 56.7 g Tube Label - Tan

sun
tegrity®

IMPECCABLE
SKIN
SUNSCREEN FOUNDATION

BROAD SPECTRUM SPF 30

SPF
30

NON-NANO ZINC OXIDE

MEDIUM COVERAGE CC CREAM
SATIN FINISH

Peptides & Vitamins C + E
Blue Light Protection
Oil Free | Vegan | Reef Friendly

NET WT 2 OZ (56.7 g)

PRINCIPAL DISPLAY PANEL - 56.7 g Tube Label - Bronze

sun
tegrity®

IMPECCABLE
SKIN
SUNSCREEN FOUNDATION

BROAD SPECTRUM SPF 30

SPF
30

NON-NANO ZINC OXIDE

MEDIUM COVERAGE CC CREAM
SATIN FINISH

Peptides & Vitamins C + E
Blue Light Protection
Oil Free | Vegan | Reef Friendly

NET WT 2 OZ (56.7 g)

PRINCIPAL DISPLAY PANEL - 56.7 g Tube Label - Nude

sun
tegrity®

IMPECCABLE
SKIN
SUNSCREEN FOUNDATION

BROAD SPECTRUM SPF 30

SPF
30

NON-NANO ZINC OXIDE

MEDIUM COVERAGE CC CREAM
SATIN FINISH

Peptides & Vitamins C + E
Blue Light Protection
Oil Free | Vegan | Reef Friendly

NET WT 2 OZ (56.7 g)

PRINCIPAL DISPLAY PANEL - 56.7 g Tube Label - Mocha

sun
tegrity®

IMPECCABLE
SKIN
SUNSCREEN FOUNDATION

BROAD SPECTRUM SPF 30

SPF
30

NON-NANO ZINC OXIDE

MEDIUM COVERAGE CC CREAM
SATIN FINISH

Peptides & Vitamins C + E
Blue Light Protection
Oil Free | Vegan | Reef Friendly

NET WT 2 OZ (56.7 g)